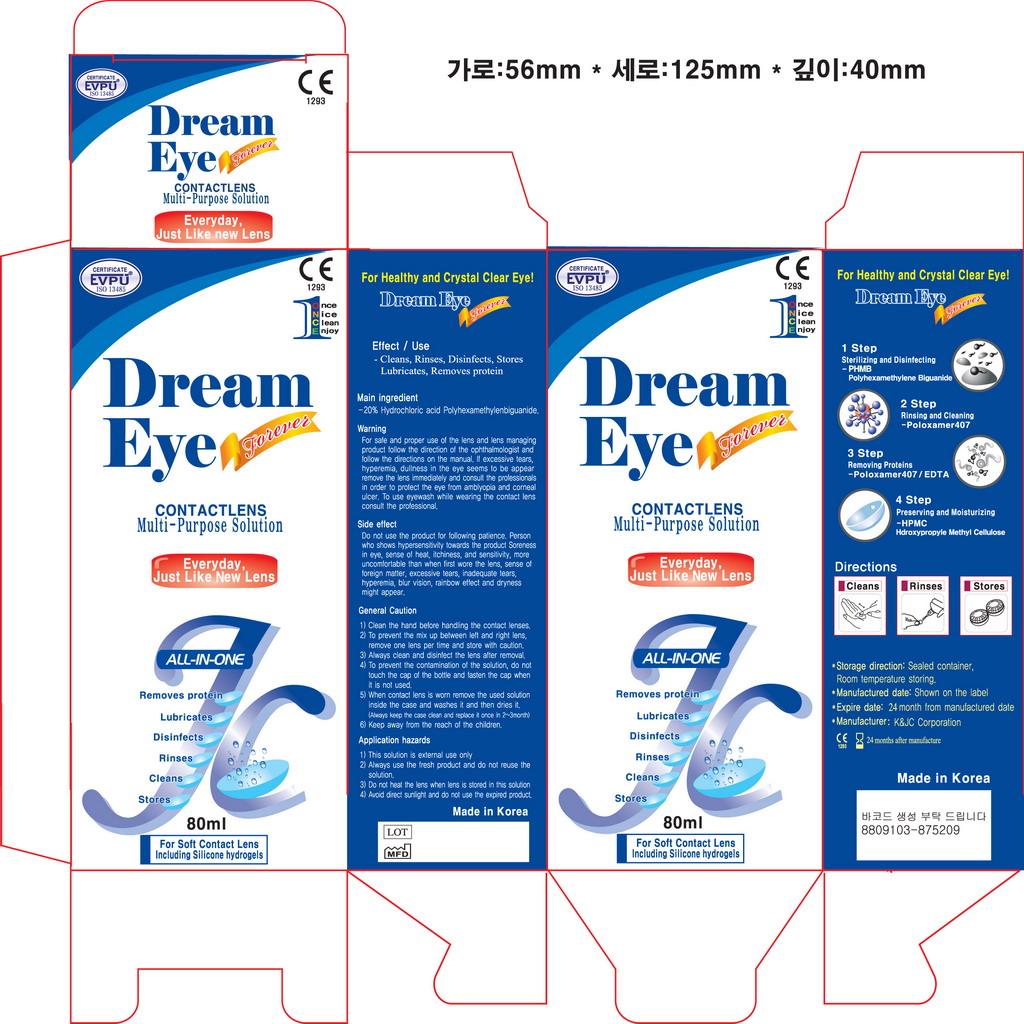 DRUG LABEL: Dream Eye
NDC: 52345-7001 | Form: LIQUID
Manufacturer: K&J.C Co., Ltd
Category: otc | Type: HUMAN OTC DRUG LABEL
Date: 20240430

ACTIVE INGREDIENTS: POLOXAMER 407 0.1 mg/1 mL
INACTIVE INGREDIENTS: WATER

Drug Facts

DESCRIPTION

Instructions for use (IFU)
Cleans, Rinses, Disinfects, Stores and Removes Protein Daily.
All Steps In One Bottle.
Directions: To clean, disinfect and remove protein daily, complete these simple steps:
STEP 1:
Place 3 drops of Dream Eye on each side of contact lens and rub for 20 seconds. No
necessary. separate daily cleaner
STEP 2:
Remove surface debris by rinsing thoroughly with Dream Eye
STEP 3:
Place cleaned contact lens in the lens case and fill with fresh Dream Eye MPS. Soak at
least four(4) hours.
CONTENTS: Dream Eye is a sterile, isotonic, buffered solution that contains poloxamer,
sodium borate, sodium chloride; preserved with Polyhexamethylenebiguanide.
ACTIONS: Cleans, loosens and removes accumulations of film, deposits and debris from
soft contact lenses. Destroys harmful micro-organisms on the surface of the
lens. Rinse, stores and rewets lenses before insertion. For dissolving of
Enzymatic Contact Lens Cleaner tablets for removal of protein deposits.
INDICATIONS(Uses): Dream Eye is indicated for use in daily cleaning, dissolving ofEnzymatic Contact Lens Cleaner tablets, rinsing and storage of daily
and extended wear soft contact lenses and chemical (not heat)
disinfection, as recommended by your eye care professional.
CONTRAINDICATIONS (Reasons not to use): If you are allergic to any ingredient in Dream
Eye, do not use this product.
WARNING: PROBLEMS WITH CONTACT LENSES AND LENS CARE PRODUCTS COULD
RESULT IN SERIOUS INJURY TO THE EYE. It is essential that you follow your
eye care practitioner's directions and all labeling instructions for proper use
and care of your lenses and lens care products, including the lens case.
☞ To avoid contamination, do not touch tip of container to any surface. Replace cap
after using.
☞ Not intended for use directly in the eye.
☞ Not for use with heat(thermal) disinfection.
PRECAUTIONS:
☞ Never re-use this solution.
☞ Keep the bottle tightly closed when not in use.
☞ Store at room temperature.
☞ Use before the expiration date marked on the bottle and carton.
☞ Keep out of the reach of childrenADVERSE REACTIONS (Problems and what to do):
The following problems may occur: eyes sting, burn or itch (irritation), comfort is less
than when lens wasfirst placed on the eye, feeling of something in the eye (foreign
body, scratched area), excessive watering (tearing) of the eye, unusual eye secretions,
redness of the eye, reduced sharpness of vision (poor visual acuity), blurred vision,
rainbows or halos around objects, sensitivity to light (photophobia), or dry eyes.
If you notice any of the above:
☞ IMMEDIATELY REMOVE YOUR LENSES.
☞ If the discomfort or problem stops, then look closely at the lens.
☞ If the lens is in any way damaged, DO NOT put the lens back on your eye. Place t
he lens in the storage case and contact your eye care practitioner.
☞ If the lens has dirt, an eyelash, or other foreigh body on it, or the problem stops
and the lens appears undamaged, thoroughly clean, rinse, and disinfect the lens,
then reinsert it.
☞ If the problem continues, IMMEDIATELY remove the lens
and consult your eye care practitioner.
If any of the above symptoms occur, a serious condition such as infection, corneal ulcer,
neovascularization or iritis may be present. Seek immediate professional identification of
the problem and prompt treatment to avoid serious eye damage.
GOOD LENS CARE PRACTICES:
☞ Always wash and rinse your hands before you handle your lenses.
☞ Clean, rinse and disinfect your lenses each time you remove them.☞ Always handle the same lens, the right or left, first in order to avoid mix-ups.
☞ After use, always empty and rinse lens case with fresh rinsing solution and allow to
air dry.
DIRECTIONS:
☞ After removing the lens, place it in the palm of your hand, and place three drops of
Daily Cleaner on each lens surface. or Soak at least four(4) hours in Dream Eye.
☞ Rub the lens for 20 seconds either in the palm of your hand using the forefinger
of the other hand, or between the thumb and forefinger. Be sure to clean each side
of the lens.
☞ Rinse the lens thoroughly by holding the lens in a steady stream of saline solution
for approximately 10 seconds.
☞ Disinfect using the procedure which your practitioner has recommended.

DOSAGE AND ADMINISTRATION

for opthalmic use only

keep our of reach of children

PURPOSE

for opthalmic use

WARNINGS

only for opthalmic use

INACTIVE INGREDIENT

water

ACTIVE INGREDIENT

POLOXAMER 407

INDICATIONS AND USAGE

for opthalmic use

Active Ingredient: Poloxamer 407